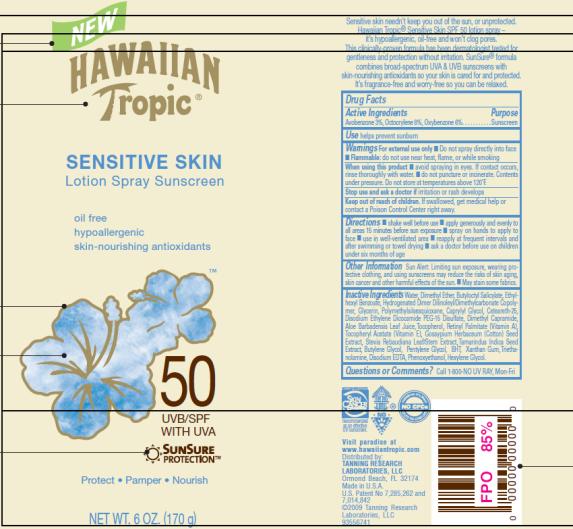 DRUG LABEL: New Hawaiian Tropic Sensitive Skin Lotion Sunscreen
NDC: 17630-2000 | Form: SPRAY
Manufacturer: Accra-Pac, Inc.
Category: otc | Type: HUMAN OTC DRUG LABEL
Date: 20100319

ACTIVE INGREDIENTS: AVOBENZONE 0.03 g/1 g; OCTOCRYLENE 0.08 g/1 g; OXYBENZONE 0.06 g/1 g
INACTIVE INGREDIENTS: WATER; GLYCERIN; CAPRYLYL GLYCOL; ALOE VERA LEAF; VITAMIN A PALMITATE; .ALPHA.-TOCOPHEROL ACETATE, D-; LEVANT COTTON OIL; STEVIA LEAF; BUTYLENE GLYCOL; PENTYLENE GLYCOL; BUTYLATED HYDROXYTOLUENE; XANTHAN GUM; TROLAMINE; EDETATE DISODIUM; PHENOXYETHANOL; HEXYLENE GLYCOL

New Hawaiian Tropic Sensitive Skin Lotion Spray Sunscreen

New Hawaiian Tropic Sensitive Skin Lotion Spray Sunscreen

Drug Facts

Active ingredients

Avobenzone 3%

Octocrylene 8%

Oxybenzone 6%

Purpose

Sunscreen

Use

helps prevent sunburn

Warnings

- For external use only
- Do not spray directly into face
- Flammable do not use near heat, flame or while smoking

While using this product

- Avoid spraying in eyes. If contact occurs rinse thoroughly with water.
- Do not puncture or incinerate. Contents under pressure. Do not store at temperatures above 120°F.

Stop use and ask a doctor

if irritation or rash develops

Keep out of reach of children.

If swallowed, get medical help or contact a Poison control center right way.

Directions

- Shake well before use
- Apply generously and evenly to all areas 15 minutes before sun exposure
- Spray on hands to apply to face
- Use in well-ventilated area
- Reapply at frequent intervals and after swimming or towel drying
- Ask a doctor before use on children under six months of age

Other Information

Sun Alert: Limiting sun exposure, wearing protective clothing, and using sunscreens may reduce the risks of skin aging, skin cancer and other harmful effects of the sun.

- May stain some fabrics.

Inactive Ingredients

Water, Dimethyl Ether, Butyloctyl Salicylate, Ethylhexyl Benzoate, Hydrogenated Dimer Dilinoleyl/Dimethylcarbonate Copolymer, Glycerin, Polymethylsilsesquioxane, Caprylyl Glycol, Ceteareth-25, Disodium Ethylene Dicocamide PEG-15 Disulfate, Dimethyl Capramide, Aloe Barbadensis Leaf Juice, Trocopherol, Retinyl Palmitate (vitamin A), Tocopheryl Acetate (vitamin E), Gossypium Herbaceum (cotton) seed extract, Stevia Rebaudiana leaf/stem extract, Tamanndus Indica Seed extract, Butylene Glycol, Pentylene glycol, BHT, Xanthan Gum, triethanolamine, Disodium EDTA, Phenoxyethanol, Hexylene Glycol,

Questions or comments?

Call 1-800-NO UV Ray, Mon-Fri

Distributed by:
Tanning Research Laboratories, LLC
Ormond Beach, FL 32174
www.hawaiiantropic.com

Principal Display Panel

New Hawaiian Tropic
Sensitive Skin
Lotion Spray Sunscreen
Oil free
Hypoallergenic
Skin-nourishing antioxidants
50 UVB/SPF with UVA
SunSure Protection TM
Protect Pamper Nourish
Net Wt. 6 oz (170g)